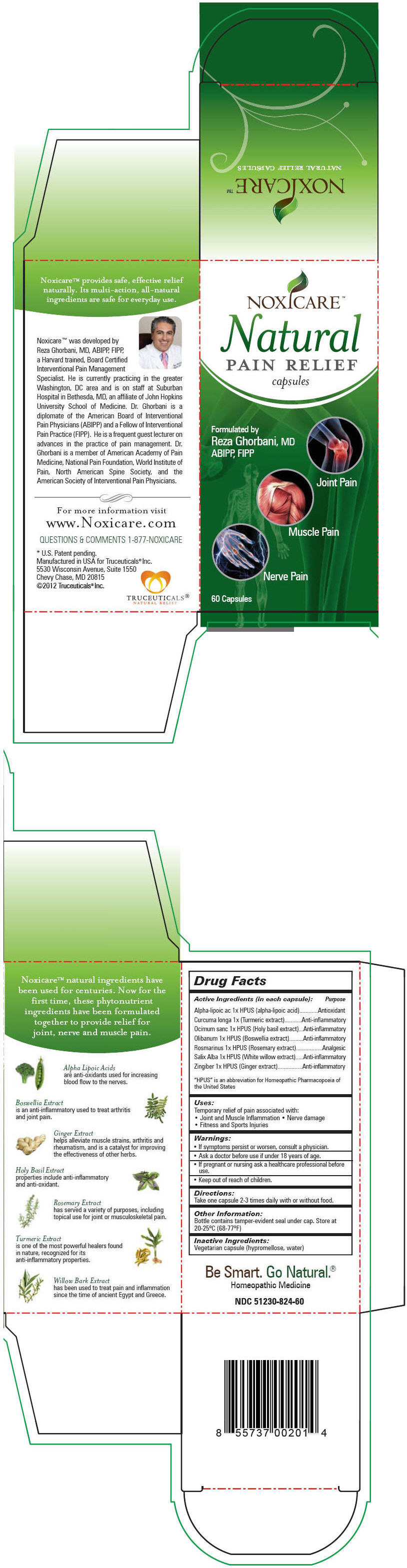 DRUG LABEL: NOXICARE 
NDC: 51230-824 | Form: CAPSULE
Manufacturer: Truceuticals, LLC
Category: homeopathic | Type: HUMAN OTC DRUG LABEL
Date: 20121220

ACTIVE INGREDIENTS: .Alpha.-Lipoic Acid 1 [hp_X]/1 1; Turmeric 1 [hp_X]/1 1; Ocimum Tenuiflorum Top 1 [hp_X]/1 1; Indian Frankincense 1 [hp_X]/1 1; Rosemary 1 [hp_X]/1 1; Salix Alba Bark 1 [hp_X]/1 1; Ginger 1 [hp_X]/1 1
INACTIVE INGREDIENTS: Hypromelloses; Water

NOXICARE™
Natural Pain Relief

Drug Facts

ACTIVE INGREDIENT

Active Ingredients (in each capsule): | Purpose
Alpha-lipoic ac 1x HPUS (alpha-lipoic acid) | Antioxidant
Curcuma longa 1x (Turmeric extract) | Anti-inflammatory
Ocimum sanc 1x HPUS (Holy basil extract) | Anti-inflammatory
Olibanum 1x HPUS (Boswellia extract) | Anti-inflammatory
Rosmarinus 1x HPUS (Rosemary extract) | Analgesic
Salix Alba 1x HPUS (White willow extract) | Anti-inflammatory
Zingiber 1x HPUS (Ginger extract) | Anti-inflammatory
"HPUS" is an abbreviation for Homeopathic Pharmacopoeia of the United States

Uses

Temporary relief of pain associated with:

- Joint and Muscle Inflammation
- Nerve damage
- Fitness and Sports Injuries

Warnings

ASK DOCTOR

- If symptoms persist or worsen, consult a physician.
- Ask a doctor before use if under 18 years of age.

PREGNANCY OR BREAST FEEDING

- If pregnant or nursing ask a healthcare professional before use.

- Keep out of reach of children.

Directions

Adults: Take one capsule 2-3 times daily with or without food. Children: Ask a doctor before use if under 18 years of age.

Other Information

Bottle contains tamper-evident seal under cap. Store at 20-25°C (68-77°F)

Inactive Ingredients

Vegetarian capsule (hypromellose, water)

QUESTIONS & COMMENTS

877-NOXICARE

Manufactured in USA for Truceuticals® Inc.
5530 Wisconsin Avenue, Suite 1550
Chevy Chase, MD 20815

PRINCIPAL DISPLAY PANEL - 60 Capsule Bottle Carton

NOXICARE™

Natural
PAIN RELIEF
capsules

Formulated by
Reza Ghorbani, MD
ABIPP, FIPP

Joint Pain

Muscle Pain

Nerve Pain

60 Capsules